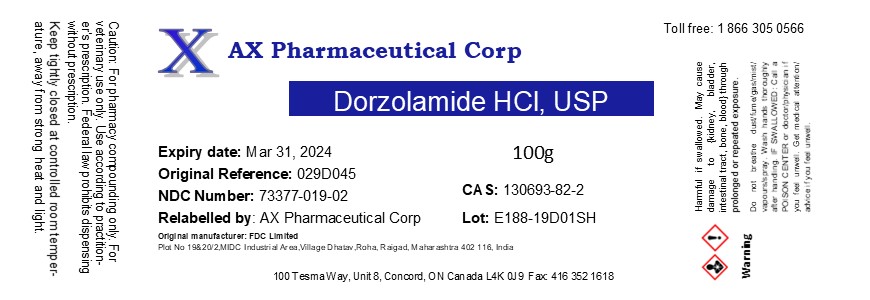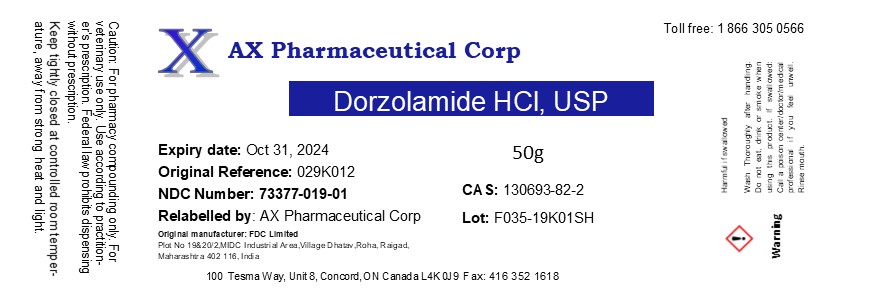 DRUG LABEL: Dorzolamide Hydrochloride
NDC: 73377-019 | Form: POWDER
Manufacturer: AX Pharmaceutical Corp
Category: other | Type: BULK INGREDIENT
Date: 20200916

ACTIVE INGREDIENTS: DORZOLAMIDE HYDROCHLORIDE 1 g/1 g

Dorzolamide Hydrochloride